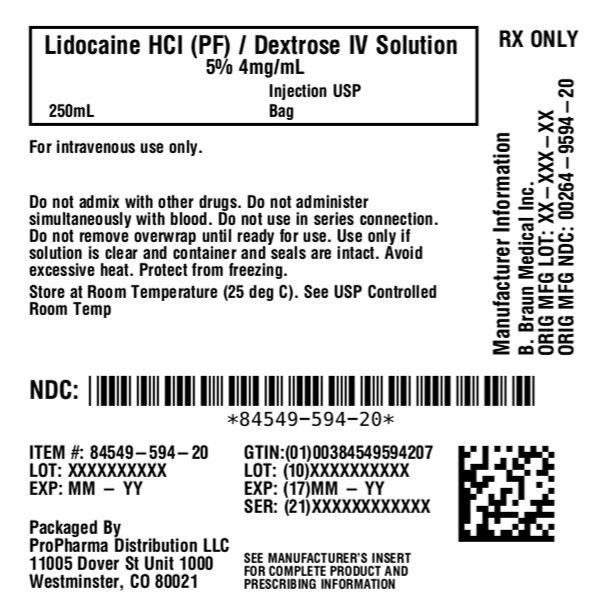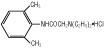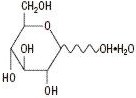 DRUG LABEL: Lidocaine Hydrochloride and Dextrose
NDC: 84549-594 | Form: INJECTION, SOLUTION
Manufacturer: ProPharma Distribution
Category: prescription | Type: HUMAN PRESCRIPTION DRUG LABEL
Date: 20260119

ACTIVE INGREDIENTS: LIDOCAINE HYDROCHLORIDE ANHYDROUS 0.4 g/100 mL; DEXTROSE MONOHYDRATE 5 g/100 mL
INACTIVE INGREDIENTS: WATER

Lidocaine Hydrochloride and
5% Dextrose Injection USP

Do not admix with other drugs.

DESCRIPTION

Lidocaine Hydrochloride and 5% Dextrose Injection USP is a sterile, nonpyrogenic solution prepared from lidocaine hydrochloride and dextrose in water for injection.

Lidocaine hydrochloride is designated chemically as 2-(Diethylamino)-2',6'-acetoxylidide monohydrochloride. The solution serves as a cardiac antiarrhythmic agent intended for intravenous use.

Composition - Each 100 mL contains:
Solution | Lidocaine Hydrochloride Anhydrous USP | Hydrous Dextrose USP | pH | Calculated Osmolarity mOsmol/liter
0.4% Lidocaine HCl and 5% Dextrose Injection USP | 0.4 g | 5 g | 4.4 (3.0–7.0) | 280
0.8% Lidocaine HCl and 5% Dextrose Injection USP | 0.8 g | 5 g | 4.2 (3.0–7.0) | 305
Water for Injection USP qs

The formulas of the active ingredients are:

Lidocaine Hydrochloride Anhydrous USP
(M.W. 270.80)

Hydrous Dextrose USP
(M.W. 198.17)

Not made with natural rubber latex, PVC or DEHP.

The plastic container is made from a multilayered film specifically developed for parenteral drugs. It contains no plasticizers and exhibits virtually no leachables. The solution contact layer is a rubberized copolymer of ethylene and propylene. The container is nontoxic and biologically inert. The container-solution unit is a closed system and is not dependent upon entry of external air during administration. The container is overwrapped to provide protection from the physical environment and to provide an additional moisture barrier when necessary.

The closure system has two ports; the one for the administration set has a tamper evident plastic protector. Refer to the Directions for Use of the container.

CLINICAL PHARMACOLOGY

Lidocaine hydrochloride exerts an antiarrhythmic effect by increasing the electric stimulation threshold of the ventricle during diastole. In usual therapeutic doses, lidocaine hydrochloride produces no change in myocardial contractility, in systemic arterial pressure, or in absolute refractory period.

About 90% of an administered dose of the drug is metabolized in the liver. The remaining 10% is excreted unchanged via the kidneys.

Lidocaine toxicity is related to systemic blood levels. The decreased clearance and longer half-life of lidocaine should be taken into consideration with prolonged (24 hour) infusions. Constant rate of infusion may result in toxic accumulation of lidocaine. Infusion should be reduced to approximately one-half to compensate for decreased rate of clearance and concomitant or prior administration of propranolol may further increase blood concentrations by as much as 30% in patients without cardiac or hepatic failure. In clinical studies, patients over 65 years showed decreased lidocaine clearance. This was partly due to the tendency of elderly patients to have lower body weight and the increased risk of cardiac failure in these patients.

This solution provides approximately 170 calories per liter.

INDICATIONS AND USAGE

Lidocaine hydrochloride administered intravenously is specifically indicated in the acute management of (1) ventricular arrhythmias occurring during cardiac manipulations, such as cardiac surgery and (2) life-threatening arrhythmias which are ventricular in origin, such as occur during acute myocardial infarction.

CONTRAINDICATIONS

Lidocaine hydrochloride is contraindicated in patients with a known history of hypersensitivity to local anesthetics of the amide type.

Lidocaine should not be used in patients with Stokes-Adams syndrome, Wolff-Parkinson-White syndrome, or with severe degrees of sinoatrial, atrioventricular, or intraventricular block.

Solutions containing dextrose may be contraindicated in patients with known allergy to corn or corn products.

WARNINGS

Constant monitoring with an electrocardiograph is essential to the proper administration of lidocaine hydrochloride intravenously. Signs of excessive depression of cardiac conductivity, such as prolongation of the PR interval, widening of the QRS interval or the appearance or aggravation of arrhythmias, should be followed by prompt cessation of the intravenous infusion of this agent. It is mandatory to have emergency resuscitative equipment and drugs immediately available to manage adverse reactions involving cardiovascular, respiratory, or central nervous systems. Occasional acceleration of ventricular rate may occur when lidocaine hydrochloride is administered to patients with atrial fibrillation. Evidence for proper usage in pediatric patients is limited. Anaphylactic reactions may occur following administration of lidocaine hydrochloride. In the case of severe reaction, discontinue the use of the drug.

Because dosages of this drug are titrated to response (see DOSAGE AND ADMINISTRATION), no additives should be made to Lidocaine Hydrochloride and 5% Dextrose Injection USP .

PRECAUTIONS

General

Caution should be employed in the repeated use of lidocaine hydrochloride in patients with severe liver or renal disease because accumulation may occur and lead to toxic phenomena, since lidocaine hydrochloride is metabolized mainly in the liver and excreted by the kidneys. The drug should also be used with caution in patients with hypovolemia and shock, and in all forms of heart block (see CONTRAINDICATIONSand WARNINGS).

In patients with sinus bradycardia or incomplete heart block, the administration of lidocaine hydrochloride intravenously for the elimination of ventricular ectopic beats without prior acceleration in heart rate (e.g.,by isoproterenol or by electric pacing) may promote more frequent and serious ventricular arrhythmias or complete heart block (see CONTRAINDICATIONS).

Most potent anesthetic agents, local anesthetics of the amide type which includes lidocaine, and muscle relaxants of both depolarizing and nondepolarizing types have been associated with malignant hyperthermia.

Care should be taken in the administration of intravenous fluids in patients with compromised myocardial function to avoid fluid overload or disturbances of serum electrolyte concentrations which might interfere with cardiac conduction or result in congestive heart failure.

Do not use plastic containers in series connection.

If administration is controlled by a pumping device, care must be taken to discontinue pumping action before the container runs dry or air embolism may result. If administration is not controlled by a pumping device, refrain from applying excessive pressure (>300mmHg) causing distortion to the container such as wringing or twisting. Such handling could result in breakage of the container.

These solutions are intended for intravenous administration using sterile equipment. It is recommended that intravenous administration apparatus be replaced at least once every 24 hours.

Use only if solution is clear and container and seals are intact.

Laboratory Tests

Clinical evaluation and periodic laboratory determinations are necessary to monitor changes in fluid balance, electrolyte concentrations, and acid-base balance during prolonged parenteral therapy or whenever the condition of the patient warrants such evaluation.

Drug Interactions

Lidocaine should be used with caution in patients with digitalis toxicity accompanied by atrioventricular block (see CONTRAINDICATIONS).

Coadministration of propranolol or cimetidine with lidocaine has been reported to reduce clearance from the plasma and may result in toxic accumulation of the drug (see CLINICAL PHARMACOLOGY).

When lidocaine is administered with other antiarrhythmic drugs such as phenytoin, procainamide, propranolol, amiodarone, or quinidine, the cardiac effects may be additive or antagonistic and toxic effects may be additive. Phenytoin may stimulate the hepatic metabolism of lidocaine, but the clinical significance of this effect is not known.

Carcinogenesis, Mutagenesis, Impairment of Fertility

Long term animal studies have not been performed to evaluate carcinogenic potential of lidocaine; nor have studies been conducted to assess the mutagenic potential of lidocaine or its potential to affect fertility.

Pregnancy

Teratogenic Effects

Reproduction studies have been performed in rats at doses up to 5 times the human dose and have revealed no evidence of harm to the fetus due to lidocaine hydrochloride. There are, however, no adequate well-controlled studies in pregnant women. Because animal reproduction studies are not always predictive of human response, this drug should be used during pregnancy only if clearly needed.

Nursing Mothers

It is not known whether this drug is excreted in human milk. Because many drugs are excreted in human milk, caution should be exercised when Lidocaine Hydrochloride and 5% Dextrose Injection USP is administered to a nursing woman.

Pediatric Use

The safety and effectiveness of lidocaine has not been established in pediatric patients (neonates to adolescents). (see WARNINGSand DOSAGE AND ADMINISTRATION.)

Geriatric Use

Lidocaine is known to be substantially excreted by the kidney, and the risk of toxic reactions to this drug may be greater in patients with impaired renal function. Because elderly patients are more likely to have decreased renal function, care should be taken in dose selection, and it may be useful to monitor renal function (see CLINICAL PHARMACOLOGYand DOSAGE AND ADMINISTRATION).

ADVERSE REACTIONS

Systemic reactions of the following types have been reported:

1. Central Nervous System: Light-headedness; drowsiness; dizziness; apprehension; euphoria; tinnitus; blurred or double vision; nausea and vomiting; sensation of heat, cold or numbness; twitching; tremors; convulsions; unconsciousness; respiratory depression and arrest.
2. Cardiovascular System: Hypotension; cardiovascular arrest; and bradycardia which may lead to cardiac arrest.
3. Hematologic Effects: methemoglobinemia
4. Allergic reactions, including anaphylactic reactions, may occur but are infrequent. There have been no reports of cross-sensitivity between lidocaine hydrochloride and procainamide or between lidocaine hydrochloride and quinidine.

OVERDOSAGE

Overdosage results in systemic toxicity (see ADVERSE REACTIONS).

DOSAGE AND ADMINISTRATION

Therapy of ventricular arrhythmias is often initiated with a single IV bolus of 1 mg/kg of Lidocaine Hydrochloride Injection USP. Following acute treatment by bolus in patients in whom arrhythmias tend to recur and who are incapable of receiving oral antiarrhythmic agents, intravenous infusion of Lidocaine Hydrochloride and 5% Dextrose Injection USP is administered continuously.

Rate of Administration

Adults (20 to 50 mcg/kg/min):

 | Average 70 kg adult
 | mg/min | mL/hr | mL/min
0.4% Lidocaine Hydrochloride and 5% Dextrose Injection USP (4 mg lidocaine hydrochloride/mL) | 1–4 | 15–60 | 0.25–1.0
0.8% Lidocaine Hydrochloride and 5% Dextrose Injection USP (8 mg lidocaine hydrochloride/mL) | 1–4 | 7.5–30 | 0.12–0.5

Pediatric Patients (30 mcg/kg/min). [Standards and Guidelines for Cardiopulmonary Resuscitation (CPR) and Emergency Cardiac Care (ECC). American Heart Association, JAMA 244 (5):453–509, 1980.]

Pharmacokinetic data indicate reduced elimination of lidocaine after prolonged infusion (24 hours) with resultant prolongation of the half-life to approximately three times that seen following a single administration. Failure to adjust the rate of infusion in keeping with this altered ability to eliminate lidocaine may result in toxic accumulation of the drug in the patient's serum. [LeLorier J, Grenon D, Latour Y, et al.: Pharmacokinetics of lidocaine after prolonged intravenous infusions in uncomplicated myocardial infarction. Ann Int Med 87:700–702, 1977.]

Intravenous infusions of lidocaine hydrochloride must be administered under constant ECG monitoring to avoid potential overdosage and toxicity. Intravenous infusion should be terminated as soon as the patient's basic cardiac rhythm appears to be stable or at the earliest signs of toxicity. It should rarely be necessary to continue intravenous infusions beyond 24 hours. As soon as possible and when indicated, patients should be changed to an oral antiarrhythmic agent for maintenance therapy.

Caution:Concentrated solutions of lidocaine hydrochloride (greater than 0.2%) should be administered by carefully calibrated infusion devices.

Pediatric Use

Therapy should be initiated with a single IV bolus of 1 mg/kg of Lidocaine Hydrochloride Injection USP. A maintenance intravenous infusion of Lidocaine Hydrochloride and 5% Dextrose Injection USP administered at a recommended infusion rate of 30 mcg/kg/min may be given.

Geriatric Use

Patients with reduced hepatic function or diminished hepatic blood flow (as in heart failure and after cardiac surgery), or those over 70 years of age should receive half the usual loading dose and also should be given lower maintenance levels of intravenous lidocaine. Patients over 65 years may benefit from dosing based upon body weight (see CLINICAL PHARMACOLOGYand PRECAUTIONS, Geriatric Use).

Lidocaine hydrochloride should not be added to blood transfusion assemblies.

Parenteral drug products should be inspected visually for particulate matter and discoloration prior to administration, whenever solution and container permit.

HOW SUPPLIED

Lidocaine Hydrochloride and 5% Dextrose Injection USP is supplied sterile and nonpyrogenic in Full Fill 250 mL EXCEL® Container.

Fill | NDC | REF | Solution
1 g Lidocaine Hydrochloride:
250 mL | 84549-594-20 |  | 0.4% Lidocaine Hydrochloride
 |  |  | and 5% Dextrose Injection USP

STORAGE AND HANDLING

Exposure of pharmaceutical products to heat should be minimized. Avoid excessive heat. Protect from freezing. It is recommended that the product be stored at room temperature (25°C); however, brief exposure up to 40°C does not adversely affect the product.

Storage in automated dispensing machines: Brief exposure up to 2 weeks to ultraviolet or fluorescent light does not adversely affect the product labeling legibility; prolonged exposure can cause fading of the red label. Rotate stock frequently.

Rx only

EXCEL is a registered trademark of B. Braun Medical Inc.

Directions for Use of EXCEL® Container

Do not admix with other drugs.

Caution:Do not use plastic containers in series connection.

To Open

Tear overwrap down at notch and remove solution container. Check for minute leaks by squeezing solution container firmly. If leaks are found, discard solution as sterility may be impaired.

NOTE:Before use, perform the following checks:

Inspect each container. Read the label. Ensure solution is the one ordered and is within the expiration date.

Invert container and carefully inspect the solution in good light for cloudiness, haze, or particulate matter.
Any container which is suspect should not be used.

Use only if solution is clear and container and seals are intact.

Preparation for Administration

1. Remove plastic protector from sterile set port at bottom of container.
2. Attach administration set. Refer to complete directions accompanying set.